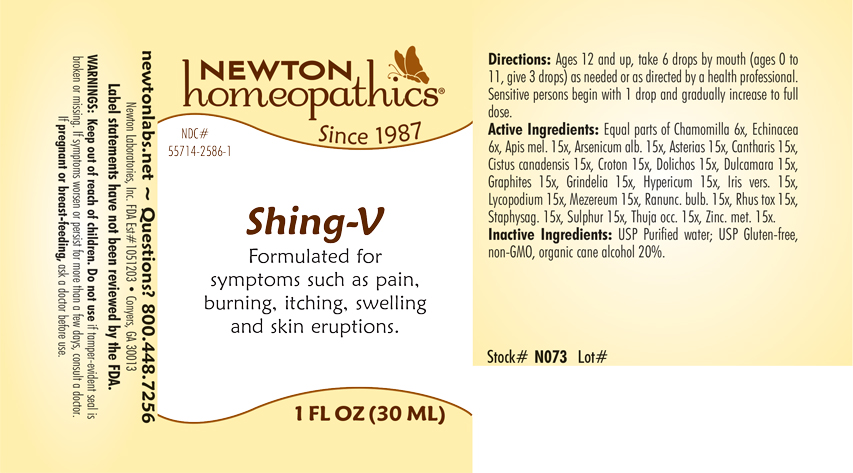 DRUG LABEL: Shing-V
NDC: 55714-2586 | Form: LIQUID
Manufacturer: Newton Laboratories, Inc.
Category: homeopathic | Type: HUMAN OTC DRUG LABEL
Date: 20240320

ACTIVE INGREDIENTS: MATRICARIA CHAMOMILLA 6 [hp_X]/1 mL; ASTERIAS RUBENS 15 [hp_X]/1 mL; LYTTA VESICATORIA 15 [hp_X]/1 mL; HELIANTHEMUM CANADENSE 15 [hp_X]/1 mL; CROTON TIGLIUM SEED 15 [hp_X]/1 mL; MUCUNA PRURIENS FRUIT TRICHOME 15 [hp_X]/1 mL; SOLANUM DULCAMARA TOP 15 [hp_X]/1 mL; GRAPHITE 15 [hp_X]/1 mL; GRINDELIA HIRSUTULA FLOWERING TOP 15 [hp_X]/1 mL; HYPERICUM PERFORATUM 15 [hp_X]/1 mL; IRIS VERSICOLOR ROOT 15 [hp_X]/1 mL; LYCOPODIUM CLAVATUM SPORE 15 [hp_X]/1 mL; DAPHNE MEZEREUM BARK 15 [hp_X]/1 mL; RANUNCULUS BULBOSUS 15 [hp_X]/1 mL; TOXICODENDRON PUBESCENS LEAF 15 [hp_X]/1 mL; DELPHINIUM STAPHISAGRIA SEED 15 [hp_X]/1 mL; SULFUR 15 [hp_X]/1 mL; THUJA OCCIDENTALIS LEAFY TWIG 15 [hp_X]/1 mL; ZINC 15 [hp_X]/1 mL; APIS MELLIFERA 15 [hp_X]/1 mL; ECHINACEA, UNSPECIFIED 6 [hp_X]/1 mL; ARSENIC TRIOXIDE 15 [hp_X]/1 mL
INACTIVE INGREDIENTS: WATER; ALCOHOL

Shing-V 2586L

INDICATIONS & USAGE SECTION

Formulated for syptoms such as pain, burning, itching, swelling and skin eruptions.

OTC - ACTIVE INGREDIENT SECTION

Equal parts of Chamomilla 6x, Echinacea 6x, Apis mel. 15x, Arsenicum alb. 15x, Asterias 15x, Cantharis 15x, Cistus canadensis 15x, Croton 15x, Dolichos 15x, Dulcamara 15x, Graphites 15x, Grindelia 15x, Hypericum 15x, Iris vers. 15x, Lycopodium 15x, Mezereum 15x, Ranunc. bulb. 15x, Rhus tox 15x, Staphysag. 15x, Sulphur 15x, Thuja occ. 15x, Zinc. met. 15x.

OTC - PURPOSE SECTION

Formulated for syptoms such as pain, burning, itching, swelling and skin eruptions.

INACTIVE INGREDIENT SECTION

USP Purified Water; USP Gluten-free, non-GMO, organic cane alcohol 20%.

QUESTIONS SECTION

newtonlabs.net – Questions? 800.448.7256

Newton Laboratories, Inc. FDA Est # 1051203 - Conyers, GA 30013

WARNINGS SECTION

WARNINGS: Keep out of reach of children. Do not use if tamper-evident seal is broken or missing. If symptoms worsen or persist for more than a few days, consult a doctor. If pregnant or breast-feeding, ask a doctor before use.

OTC - PREGNANCY OR BREAST FEEDING SECTION

If pregnant or breast-feeding, ask a doctor before use.

OTC - KEEP OUT OF REACH OF CHILDREN SECTION

Keep out of reach of children.

DOSAGE & ADMINISTRATION SECTION

Directions: Ages 12 and up, take 6 drops by mouth (ages 0 to 11, give 3 drops) as need or as directed by a health professional. Sensitive person begin with 1 drop and gradually increase to full dose.